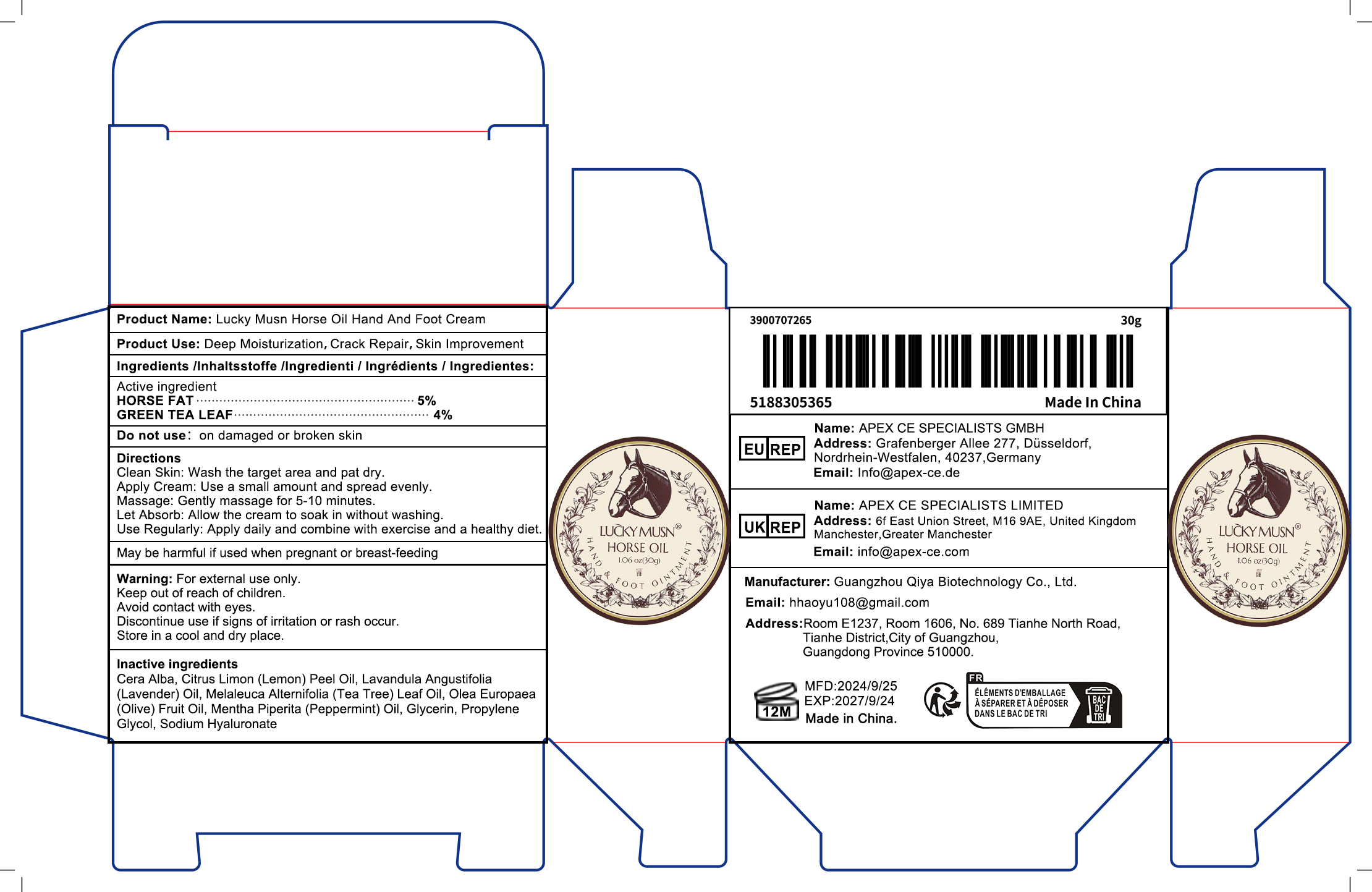 DRUG LABEL: Lucky Musn Horse Oil Hand And Foot Cream
NDC: 84793-007 | Form: POULTICE
Manufacturer: Guangzhou Qiya Biotechnology Co., Ltd
Category: otc | Type: HUMAN OTC DRUG LABEL
Date: 20241127

ACTIVE INGREDIENTS: HORSE FAT 2 g/2 g; GREEN TEA LEAF 2 g/2 g
INACTIVE INGREDIENTS: SODIUM HYALURONATE 2 g/2 g; LAVANDULA ANGUSTIFOLIA (LAVENDER) OIL 2 g/2 g; MELALEUCA ALTERNIFOLIA (TEA TREE) LEAF OIL 2 g/2 g

Purpose

Deep Moisturization，Crack Repair，Skin Improvement

Uses

Gently massage into feet, focusing on dry areas. Allow to absorb before putting on socks. Recommended for daily use.

Warnings

For external use only. Keep out of reach of children.Avoid contact with eyes. Discontinue use if signs of irritation or rash occur.Store in a cool and dry place.

Stop use and ask a doctor if

rash occurs

Do not use

Skin Damage，Allergic Reactions，Pregnant Women

When using this product

keep out of eyes. Rinse with water to remove

Keep out of reach of children.

If swallowed, get medical help or contact a Poison Control Center right away.

Dosage and Management

Recommended Amount: Approximately 10 grams per application.

Frequency of Use: Apply twice daily, morning and night.

Application Method: Clean the target area, apply evenly, and massage gently for 5-10 minutes.

Storage Conditions: Keep in a cool, dry place away from direct sunlight.

Allergy Test: Conduct a patch test on a small area before full use.

Warning: Discontinue use if any adverse reactions occur and consult a professional.

inactive ingredients

Cera Alba 5%

Citrus Limon (Lemon) Peel Oil 11%

Lavandula Angustifolia (Lavender) Oil 8%

Melaleuca Alternifolia (Tea Tree) Leaf Oil 12%

Olea Europaea (Olive) Fruit Oil 8%

Mentha Piperita (Peppermint) Oil 7%

Glycerin 9%

Propylene Glycol 3%

Sodium Hyaluronate 2%